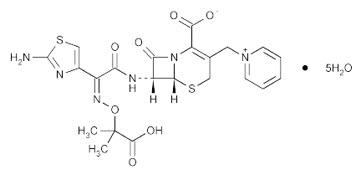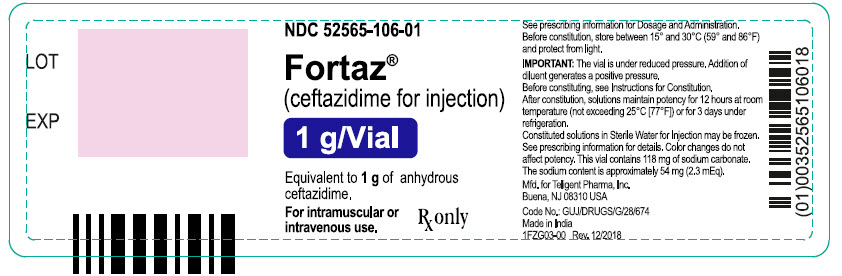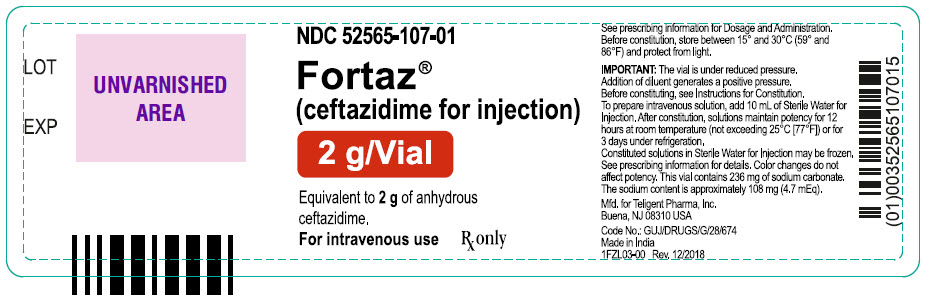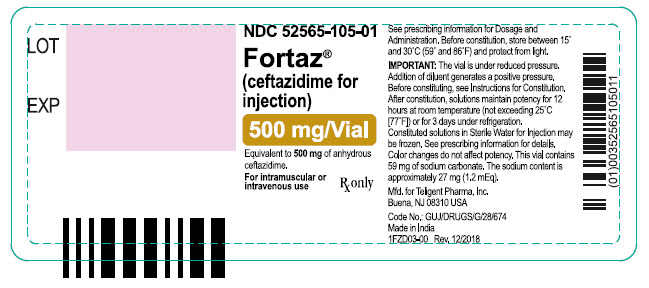 DRUG LABEL: FORTAZ 
NDC: 52565-105 | Form: INJECTION, POWDER, FOR SOLUTION
Manufacturer: Teligent Pharma, Inc.
Category: prescription | Type: HUMAN PRESCRIPTION DRUG LABEL
Date: 20170728

ACTIVE INGREDIENTS: CEFTAZIDIME 100 mg/1 mL
INACTIVE INGREDIENTS: SODIUM CARBONATE

FORTAZ®
(ceftazidime for injection)

Rx only
For Intravenous or Intramuscular Use

To reduce the development of drug-resistant bacteria and maintain the effectiveness of FORTAZ and other antibacterial drugs, FORTAZ should be used only to treat infections that are proven or strongly suspected to be caused by bacteria

DESCRIPTION

Ceftazidime is a semisynthetic, broad-spectrum, beta-lactam antibacterial drug for parenteral administration. It is the pentahydrate of pyridinium, 1-[[7-[[(2-amino-4-thiazolyl)[(1-carboxy-1-methylethoxy)imino]acetyl]amino]-2-carboxy-8-oxo-5-thia-1-azabicyclo[4.2.0]oct-2-en-3-yl]methyl]-, hydroxide, inner salt, [6R-[6α,7β(Z)]]. It has the following structure:

The molecular formula is C22H22N6O7S2•5H2O, representing a molecular weight of 636.65.

FORTAZ is a sterile, dry-powdered mixture of ceftazidime pentahydrate and sodium carbonate. The sodium carbonate at a concentration of 118 mg/g of ceftazidime activity has been admixed to facilitate dissolution. The total sodium content of the mixture is approximately 54 mg (2.3 mEq)/g of ceftazidime activity.

FORTAZ in sterile crystalline form is supplied in single-dose vials equivalent to 500 mg, 1 g, or 2 g of anhydrous ceftazidime.
Solutions of FORTAZ range in color from light yellow to amber, depending on the diluent and volume used. The pH of freshly constituted solutions usually ranges from 5 to 8.

CLINICAL PHARMACOLOGY

After IV administration of 500-mg and 1-g doses of ceftazidime over 5 minutes to normal adult male volunteers, mean peak serum concentrations of 45 and 90 mcg/mL, respectively, were achieved. After IV infusion of 500-mg, 1-g, and 2-g doses of ceftazidime over 20 to 30 minutes to normal adult male volunteers, mean peak serum concentrations of 42, 69, and 170 mcg/mL, respectively, were achieved. The average serum concentrations following IV infusion of 500-mg, 1-g, and 2-g doses to these volunteers over an 8-hour interval are given in Table 1.

Table 1 Average Serum Concentrations of Ceftazidime
Ceftazidime | Serum Concentrations (mcg/mL)
IV Dose | 0.5 hr | 1 hr | 2 hr | 4 hr | 8 hr
500 mg | 42 | 25 | 12 | 6 | 2
1 g | 60 | 39 | 23 | 11 | 3
2 g | 129 | 75 | 42 | 13 | 5

The absorption and elimination of ceftazidime were directly proportional to the size of the dose. The half-life following IV administration was approximately 1.9 hours. Less than 10% of ceftazidime was protein bound. The degree of protein binding was independent of concentration. There was no evidence of accumulation of ceftazidime in the serum in individuals with normal renal function following multiple IV doses of 1 and 2 g every 8 hours for 10 days.

Following intramuscular (IM) administration of 500-mg and 1-g doses of ceftazidime to normal adult volunteers, the mean peak serum concentrations were 17 and 39 mcg/mL, respectively, at approximately 1 hour. Serum concentrations remained above 4 mcg/mL for 6 and 8 hours after the IM administration of 500-mg and 1-g doses, respectively. The half-life of ceftazidime in these volunteers was approximately 2 hours.

The presence of hepatic dysfunction had no effect on the pharmacokinetics of ceftazidime in individuals administered 2 g intravenously every 8 hours for 5 days. Therefore, a dosage adjustment from the normal recommended dosage is not required for patients with hepatic dysfunction, provided renal function is not impaired.

Approximately 80% to 90% of an IM or IV dose of ceftazidime is excreted unchanged by the kidneys over a 24-hour period. After the IV administration of single 500-mg or 1-g doses, approximately 50% of the dose appeared in the urine in the first 2 hours. An additional 20% was excreted between 2 and 4 hours after dosing, and approximately another 12% of the dose appeared in the urine between 4 and 8 hours later. The elimination of ceftazidime by the kidneys resulted in high therapeutic concentrations in the urine.

The mean renal clearance of ceftazidime was approximately 100 mL/min. The calculated plasma clearance of approximately 115 mL/min indicated nearly complete elimination of ceftazidime by the renal route. Administration of probenecid before dosing had no effect on the elimination kinetics of ceftazidime. This suggested that ceftazidime is eliminated by glomerular filtration and is not actively secreted by renal tubular mechanisms.

Since ceftazidime is eliminated almost solely by the kidneys, its serum half-life is significantly prolonged in patients with impaired renal function. Consequently, dosage adjustments in such patients as described in the DOSAGE AND ADMINISTRATION section are suggested.

Therapeutic concentrations of ceftazidime are achieved in the following body tissues and fluids.

Table 2. Ceftazidime Concentrations in Body Tissues and Fluids
Tissue or Fluid | Dose/Route | No. of Patients | Time of Sample Postdose | Average Tissue; or Fluid Level; (mcg/mL or mcg/g)
Urine | 500 mg IM | 6 | 0-2 hr | 2,100.0
 | 2 g IV | 6 | 0-2 hr | 12,000.0
Bile | 2 g IV | 3 | 90 min | 36.4
Synovial fluid | 2 g IV | 13 | 2 hr | 25.6
Peritoneal fluid | 2 g IV | 8 | 2 hr | 48.6
Sputum | 1 g IV | 8 | 1 hr | 9.0
Cerebrospinal fluid | 2 g q8hr IV | 5 | 120 min | 9.8
(inflamed meninges) | 2 g q8hr IV | 6 | 180 min | 9.4
Aqueous humor | 2 g IV | 13 | 1-3 hr | 11.0
Blister fluid | 1 g IV | 7 | 2-3 hr | 19.7
Lymphatic fluid | 1 g IV | 7 | 2-3 hr | 23.4
Bone | 2 g IV | 8 | 0.67 hr | 31.1
Heart muscle | 2 g IV | 35 | 30-280 min | 12.7
Skin | 2 g IV | 22 | 30-180 min | 6.6
Skeletal muscle | 2 g IV | 35 | 30-280 min | 9.4
Myometrium | 2 g IV | 31 | 1-2 hr | 18.7

Microbiology

Mechanism of Action

Ceftazidime is a bactericidal agent that acts by inhibition of bacterial cell wall synthesis. Ceftazidime has activity in the presence of some beta-lactamases, both penicillinases and cephalosporinases, of Gram-negative and Gram-positive bacteria.

Mechanism of Resistance

Resistance to ceftazidime is primarily through hydrolysis by beta-lactamase, alteration of penicillin-binding proteins (PBPs), and decreased permeability.

Interaction with Other Antimicrobials

In an in vitro study antagonistic effects have been observed with the combination of chloramphenicol and ceftazidime.

Ceftazidime has been shown to be active against most isolates of the following bacteria, both in vitro and in clinical infections as described in the INDICATIONS AND USAGE section:

Gram-negative bacteria

- Citrobacter species
- Enterobacter species
- Escherichia coli
- Klebsiella species
- Haemophilus influenzae
- Neisseria meningitidis
- Proteus mirabilis
- Proteus vulgaris
- Pseudomonas aeruginosa
- Serratia species

Gram-positive bacteria

- Staphylococcus aureus
- Streptococcus pneumoniae
- Streptococcus pyogenes
- Streptococcus agalactiae

Anaerobic bacteria

- Bacteroides species (Note: many isolates of Bacteroides species are resistant)

The following in vitro data are available, but their clinical significance is unknown. At least 90 percent of the following microorganisms exhibit an in vitro minimum inhibitory concentration (MIC) less than or equal to the susceptible breakpoint for ceftazidime. However, the efficacy of ceftazidime in treating clinical infections due to these microorganisms has not been established in adequate and well-controlled clinical trials.

Gram-negative bacteria

- Acinetobacter species
- Citrobacter diversus
- Citrobacter freundii
- Providencia species (including Providencia rettgeri)
- Salmonella species
- Shigella species
- Haemophilus parainfluenzae
- Morganella morganii
- Neisseria gonorrhoeae
- Yersinia enterocolitica

Gram-positive bacteria

- Staphylococcus epidermidis

Anaerobic bacteria

- Clostridium species (Not including Clostridium difficile)
- Peptostreptococcus species

Susceptibility Testing
For specific information regarding susceptibility test interpretive criteria and associated test methods and quality control standards recognized by FDA for this drug, please see: https://www.fda.gov/STIC.

INDICATIONS AND USAGE

FORTAZ is indicated for the treatment of patients with infections caused by susceptible strains of the designated organisms in the following diseases:

1. Lower Respiratory Tract Infections, including pneumonia, caused by Pseudomonas aeruginosa and other Pseudomonas spp.; Haemophilus influenzae, including ampicillin-resistant strains; Klebsiella spp.; Enterobacter spp.; Proteus mirabilis; Escherichia coli; Serratia spp.; Citrobacter spp.; Streptococcus pneumoniae; and Staphylococcus aureus (methicillin-susceptible strains).
2. Skin and Skin-Structure Infections caused by Pseudomonas aeruginosa; Klebsiella spp.; Escherichia coli; Proteus spp., including Proteus mirabilis and indole-positive Proteus; Enterobacter spp.; Serratia spp.; Staphylococcus aureus (methicillin-susceptible strains); and Streptococcus pyogenes (group A beta-hemolytic streptococci).
3. Urinary Tract Infections, both complicated and uncomplicated, caused by Pseudomonas aeruginosa; Enterobacter spp.; Proteus spp., including Proteus mirabilis and indole-positive Proteus; Klebsiella spp.; and Escherichia coli.
4. Bacterial Septicemia caused by Pseudomonas aeruginosa, Klebsiella spp., Haemophilus influenzae, Escherichia coli, Serratia spp., Streptococcus pneumoniae, and Staphylococcus aureus (methicillin-susceptible strains).
5. Bone and Joint Infections caused by Pseudomonas aeruginosa, Klebsiella spp., Enterobacter spp., and Staphylococcus aureus (methicillin-susceptible strains).
6. Gynecologic Infections, including endometritis, pelvic cellulitis, and other infections of the female genital tract caused by Escherichia coli.
7. Intra-abdominal Infections, including peritonitis caused by Escherichia coli, Klebsiella spp., and Staphylococcus aureus (methicillin-susceptible strains) and polymicrobial infections caused by aerobic and anaerobic organisms and Bacteroides spp. (many strains of Bacteroides fragilis are resistant).
8. Central Nervous System Infections, including meningitis, caused by Haemophilus influenzae and Neisseria meningitidis. Ceftazidime has also been used successfully in a limited number of cases of meningitis due to Pseudomonas aeruginosa and Streptococcus pneumoniae.

FORTAZ may be used alone in cases of confirmed or suspected sepsis. Ceftazidime has been used successfully in clinical trials as empiric therapy in cases where various concomitant therapies with other antibacterial drugs have been used.

FORTAZ may also be used concomitantly with other antibacterial drugs, such as aminoglycosides, vancomycin, and clindamycin; in severe and life-threatening infections; and in the immunocompromised patient. When such concomitant treatment is appropriate, prescribing information in the labeling for the other antibacterial drugs should be followed. The dose depends on the severity of the infection and the patient's condition.

To reduce the development of drug-resistant bacteria and maintain the effectiveness of FORTAZ and other antibacterial drugs, FORTAZ should be used only to treat infections that are proven or strongly suspected to be caused by susceptible bacteria. When culture and susceptibility information are available, they should be considered in selecting or modifying antibacterial therapy. In the absence of such data, local epidemiology and susceptibility patterns may contribute to the empiric selection of therapy.

CONTRAINDICATIONS

FORTAZ is contraindicated in patients who have shown hypersensitivity to ceftazidime or the cephalosporin group of antibacterial drugs.

WARNINGS

BEFORE THERAPY WITH FORTAZ IS INSTITUTED, CAREFUL INQUIRY SHOULD BE MADE TO DETERMINE WHETHER THE PATIENT HAS HAD PREVIOUS HYPERSENSITIVITY REACTIONS TO CEFTAZIDIME, CEPHALOSPORINS, PENICILLINS, OR OTHER DRUGS. IF THIS PRODUCT IS TO BE GIVEN TO PENICILLIN-SENSITIVE PATIENTS, CAUTION SHOULD BE EXERCISED BECAUSE CROSS-HYPERSENSITIVITY AMONG BETA-LACTAM ANTIBACTERIAL DRUGS HAS BEEN CLEARLY DOCUMENTED AND MAY OCCUR IN UP TO 10% OF PATIENTS WITH A HISTORY OF PENICILLIN ALLERGY. IF AN ALLERGIC REACTION TO FORTAZ OCCURS, DISCONTINUE THE DRUG. SERIOUS ACUTE HYPERSENSITIVITY REACTIONS MAY REQUIRE TREATMENT WITH EPINEPHRINE AND OTHER EMERGENCY MEASURES, INCLUDING OXYGEN, IV FLUIDS, IV ANTIHISTAMINES, CORTICOSTEROIDS, PRESSOR AMINES, AND AIRWAY MANAGEMENT, AS CLINICALLY INDICATED.

Clostridium difficile associated diarrhea (CDAD) has been reported with use of nearly all antibacterial agents, including FORTAZ, and may range in severity from mild diarrhea to fatal colitis. Treatment with antibacterial agents alters the normal flora of the colon leading to overgrowth of C. difficile.

C. difficile produces toxins A and B which contribute to the development of CDAD. Hypertoxin producing strains of C. difficile cause increased morbidity and mortality, as these infections can be refractory to antimicrobial therapy and may require colectomy. CDAD must be considered in all patients who present with diarrhea following antibiotic use. Careful medical history is necessary since CDAD has been reported to occur over two months after the administration of antibacterial agents.

If CDAD is suspected or confirmed, ongoing antibiotic use not directed against C. difficile may need to be discontinued. Appropriate fluid and electrolyte management, protein supplementation, antibiotic treatment of C. difficile, and surgical evaluation should be instituted as clinically indicated.

Elevated levels of ceftazidime in patients with renal insufficiency can lead to seizures, nonconvulsive status epilepticus (NCSE), encephalopathy, coma, asterixis, neuromuscular excitability, and myoclonia (see PRECAUTIONS).

PRECAUTIONS

General

High and prolonged serum ceftazidime concentrations can occur from usual dosages in patients with transient or persistent reduction of urinary output because of renal insufficiency. The total daily dosage should be reduced when ceftazidime is administered to patients with renal insufficiency (see DOSAGE AND ADMINISTRATION). Elevated levels of ceftazidime in these patients can lead to seizures, nonconvulsive status epilepticus, encephalopathy, coma, asterixis, neuromuscular excitability, and myoclonia. Continued dosage should be determined by degree of renal impairment, severity of infection, and susceptibility of the causative organisms.

As with other antibacterial drugs, prolonged use of FORTAZ may result in overgrowth of nonsusceptible organisms. Repeated evaluation of the patient's condition is essential. If superinfection occurs during therapy, appropriate measures should be taken.

Inducible type I beta-lactamase resistance has been noted with some organisms (e.g., Enterobacter spp., Pseudomonas spp., and Serratia spp.). As with other extended-spectrum beta-lactam antibacterial drugs, resistance can develop during therapy, leading to clinical failure in some cases. When treating infections caused by these organisms, periodic susceptibility testing should be performed when clinically appropriate. If patients fail to respond to monotherapy, an aminoglycoside or similar agent should be considered.

Cephalosporins may be associated with a fall in prothrombin activity. Those at risk include patients with renal and hepatic impairment, or poor nutritional state, as well as patients receiving a protracted course of antimicrobial therapy.

Prothrombin time should be monitored in patients at risk and exogenous vitamin K administered.

FORTAZ should be prescribed with caution in individuals with a history of gastrointestinal disease, particularly colitis.

Distal necrosis can occur after inadvertent intra-arterial administration of ceftazidime.

Prescribing FORTAZ in the absence of a proven or strongly suspected bacterial infection or a prophylactic indication is unlikely to provide benefit to the patient and increases the risk of the development of drug-resistant bacteria.

Information for Patients

Patients should be counseled that antibacterial drugs, including FORTAZ, should only be used to treat bacterial infections. They do not treat viral infections (e.g., the common cold). When FORTAZis prescribed to treat a bacterial infection, patients should be told that although it is common to feel better early in the course of therapy, the medication should be taken exactly as directed. Skipping doses or not completing the full course of therapy may: (1) decrease the effectiveness of the immediate treatment, and (2) increase the likelihood that bacteria will develop resistance and will not be treatable by FORTAZ or other antibacterial drugs in the future.

Diarrhea is a common problem caused by antibacterial drugs which usually ends when the antibacterial drugs are discontinued. Sometimes after starting treatment with antibacterial drugs, patients can develop watery and bloody stools (with or without stomach cramps and fever) even as late as 2 or more months after having taken the last dose of the antibiotic. If this occurs, patients should contact their physician as soon as possible.

Drug Interactions

Nephrotoxicity has been reported following concomitant administration of cephalosporins with aminoglycoside antibacterial drugs or potent diuretics such as furosemide. Renal function should be carefully monitored, especially if higher dosages of the aminoglycosides are to be administered or if therapy is prolonged, because of the potential nephrotoxicity and ototoxicity of aminoglycoside antibacterial drugs. Nephrotoxicity and ototoxicity were not noted when ceftazidime was given alone in clinical trials.

Chloramphenicol has been shown to be antagonistic to beta-lactam antibacterial drugs, including ceftazidime, based on in vitro studies and time kill curves with enteric gram-negative bacilli. Due to the possibility of antagonism in vivo, particularly when bactericidal activity is desired, this drug combination should be avoided.

In common with other antibacterial drugs, ceftazidime may affect the gut flora, leading to lower estrogen reabsorption and reduced efficacy of combined oral estrogen/progesterone contraceptives.

Drug/Laboratory Test Interactions

The administration of ceftazidime may result in a false-positive reaction for glucose in the urine when using Clinitest® tablets, Benedict's solution, or Fehling's solution. It is recommended that glucose tests based on enzymatic glucose oxidase reactions (such as CLINISTIX®) be used.

Carcinogenesis, Mutagenesis, Impairment of Fertility

Long-term studies in animals have not been performed to evaluate carcinogenic potential. However, a mouse micronucleus test and an Ames test were both negative for mutagenic effects.

Pregnancy

Teratogenic Effects

Pregnancy Category B. Reproduction studies have been performed in mice and rats at doses up to 40 times the human dose and have revealed no evidence of impaired fertility or harm to the fetus due to FORTAZ. There are, however, no adequate and well-controlled studies in pregnant women. Because animal reproduction studies are not always predictive of human response, this drug should be used during pregnancy only if clearly needed.

Nursing Mothers

Ceftazidime is excreted in human milk in low concentrations. Caution should be exercised when FORTAZ® is administered to a nursing woman.

Pediatric Use

See DOSAGE AND ADMINISTRATION.

Geriatric Use

Of the 2,221 subjects who received ceftazidime in 11 clinical studies, 824 (37%) were 65 and older while 391 (18%) were 75 and older. No overall differences in safety or effectiveness were observed between these subjects and younger subjects, and other reported clinical experience has not identified differences in responses between the elderly and younger patients, but greater susceptibility of some older individuals to drug effects cannot be ruled out. This drug is known to be substantially excreted by the kidney, and the risk of toxic reactions to this drug may be greater in patients with impaired renal function. Because elderly patients are more likely to have decreased renal function, care should be taken in dose selection, and it may be useful to monitor renal function (see DOSAGE AND ADMINISTRATION).

ADVERSE REACTIONS

Ceftazidime is generally well tolerated. The incidence of adverse reactions associated with the administration of ceftazidime was low in clinical trials. The most common were local reactions following IV injection and allergic and gastrointestinal reactions. Other adverse reactions were encountered infrequently. No disulfiram-like reactions were reported.

The following adverse effects from clinical trials were considered to be either related to ceftazidime therapy or were of uncertain etiology:

Local Effects, reported in fewer than 2% of patients, were phlebitis and inflammation at the site of injection (1 in 69 patients).

Hypersensitivity Reactions, reported in 2% of patients, were pruritus, rash, and fever. Immediate reactions, generally manifested by rash and/or pruritus, occurred in 1 in 285 patients. Toxic epidermal necrolysis, Stevens-Johnson syndrome, and erythema multiforme have also been reported with cephalosporin antibacterial drugs, including ceftazidime. Angioedema and anaphylaxis (bronchospasm and/or hypotension) have been reported very rarely.

Gastrointestinal Symptoms, reported in fewer than 2% of patients, were diarrhea (1 in 78), nausea (1 in 156), vomiting (1 in 500), and abdominal pain (1 in 416). The onset of pseudomembranous colitis symptoms may occur during or after treatment (see WARNINGS).

Central Nervous System Reactions (fewer than 1%) included headache, dizziness, and paresthesia. Seizures have been reported with several cephalosporins, including ceftazidime. In addition, encephalopathy, coma, asterixis, neuromuscular excitability, and myoclonia have been reported in renally impaired patients treated with unadjusted dosing regimens of ceftazidime (see PRECAUTIONS: General).

Less Frequent Adverse Events (fewer than 1%) were candidiasis (including oral thrush) and vaginitis.

Hematologic: Rare cases of hemolytic anemia have been reported.

Laboratory Test Changes noted during clinical trials with FORTAZ were transient and included: eosinophilia (1 in 13), positive Coombs test without hemolysis (1 in 23), thrombocytosis (1 in 45), and slight elevations in one or more of the hepatic enzymes, aspartate aminotransferase (AST, SGOT) (1 in 16), alanine aminotransferase (ALT, SGPT) (1 in 15), LDH (1 in 18), GGT (1 in 19), and alkaline phosphatase (1 in 23). As with some other cephalosporins, transient elevations of blood urea, blood urea nitrogen, and/or serum creatinine were observed occasionally. Transient leukopenia, neutropenia, agranulocytosis, thrombocytopenia, and lymphocytosis were seen very rarely.

Postmarketing Experience with FORTAZ Products

In addition to the adverse events reported during clinical trials, the following events have been observed during clinical practice in patients treated with FORTAZ® and were reported spontaneously. For some of these events, data are insufficient to allow an estimate of incidence or to establish causation.

General

Anaphylaxis; allergic reactions, which, in rare instances, were severe (e.g., cardiopulmonary arrest); urticaria; pain at injection site.

Hepatobiliary Tract

Hyperbilirubinemia, jaundice.

Renal and Genitourinary

Renal impairment.

Cephalosporin-Class Adverse Reactions

In addition to the adverse reactions listed above that have been observed in patients treated with ceftazidime, the following adverse reactions and altered laboratory tests have been reported for cephalosporin-class antibacterial drugs:

Adverse Reactions

Colitis, toxic nephropathy, hepatic dysfunction including cholestasis, aplastic anemia, hemorrhage.

Altered Laboratory Tests

Prolonged prothrombin time, false-positive test for urinary glucose, pancytopenia.

To report SUSPECTED ADVERSE REACTIONS, contact Teligent Pharma, Inc. at 1-856-697-1441, or FDA at 1-800-FDA-1088 or www.fda.gov/medwatch.

OVERDOSAGE

Ceftazidime overdosage has occurred in patients with renal failure. Reactions have included seizure activity, encephalopathy, asterixis, neuromuscular excitability, and coma. Patients who receive an acute overdosage should be carefully observed and given supportive treatment. In the presence of renal insufficiency, hemodialysis or peritoneal dialysis may aid in the removal of ceftazidime from the body.

DOSAGE AND ADMINISTRATION

Dosage

The usual adult dosage is 1 gram administered intravenously or intramuscularly every 8 to 12 hours. The dosage and route should be determined by the susceptibility of the causative organisms, the severity of infection, and the condition and renal function of the patient.

The guidelines for dosage of FORTAZ® are listed in Table 3. The following dosage schedule is recommended.

Table 3. Recommended Dosage Schedule
 | Dose | Frequency
Adults
Usual recommended dosage | 1 gram intravenous or intramuscular | every 8 to 12 hours
Uncomplicated urinary tract infections | 250 mg intravenous or intramuscular | every 12 hours
Bone and joint infections | 2 grams intravenous | every 12 hours
Complicated urinary tract infections | 500 mg intravenous or intramuscular | every 8 to 12 hours
Uncomplicated pneumonia; mild skin and skin-structure infections | 500 mg to 1 gram intravenous or intramuscular | every 8 hours
Serious gynecologic and intra-abdominal infections | 2 grams intravenous | every 8 hours
Meningitis | 2 grams intravenous | every 8 hours
Very severe life-threatening infections, especially in immunocompromised patients | 2 grams intravenous | every 8 hours
Lung infections caused by Pseudomonas spp. in patients with cystic fibrosis with normal renal function [Although clinical improvement has been shown, bacteriologic cures cannot be expected in patients with chronic respiratory disease and cystic fibrosis.] | 30 to 50 mg/kg intravenous to a maximum of 6 grams per day | every 8 hours
Neonates (0-4 weeks) | 30 mg/kg intravenous | every 12 hours
Infants and children; (1 month-12 years) | 30 to 50 mg/kg intravenous to a maximum of 6 grams per day [The higher dose should be reserved for immunocompromised pediatric patients or pediatric patients with cystic fibrosis or meningitis.] | every 8 hours

Impaired Hepatic Function

No adjustment in dosage is required for patients with hepatic dysfunction.

Impaired Renal Function

Ceftazidime is excreted by the kidneys, almost exclusively by glomerular filtration. Therefore, in patients with impaired renal function (glomerular filtration rate [GFR] <50 mL/min), it is recommended that the dosage of ceftazidime be reduced to compensate for its slower excretion. In patients with suspected renal insufficiency, an initial loading dose of 1 gram of FORTAZ® may be given. An estimate of GFR should be made to determine the appropriate maintenance dosage. The recommended dosage is presented in Table 4.

Table 4. Recommended Maintenance Dosages of FORTAZ® in Renal Insufficiency
NOTE: IF THE DOSE RECOMMENDED IN Table 3 ABOVE IS LOWER THAN THAT RECOMMENDED FOR PATIENTS WITH RENAL INSUFFICIENCY AS OUTLINED IN Table 4, THE LOWER DOSE SHOULD BE USED.
Creatinine Clearance (mL/min) | Recommended Unit Dose; of FORTAZ® | Frequency of Dosing
50-31 | 1 gram | every 12 hours
30-16 | 1 gram | every 24 hours
15-6 | 500 mg | every 24 hours
less than 5 | 500 mg | every 48 hours

When only serum creatinine is available, the following formula (Cockcroft's equation)^1 may be used to estimate creatinine clearance. The serum creatinine should represent a steady state of renal function:

Males: Creatinine clearance (mL/min) = | Weight (kg) x (140 - age); 72 x serum creatinine (mg/dL)
Females: 0.85 x male value

In patients with severe infections who would normally receive 6 grams of FORTAZ daily were it not for renal insufficiency, the unit dose given in the table above may be increased by 50% or the dosing frequency may be increased appropriately. Further dosing should be determined by therapeutic monitoring, severity of the infection, and susceptibility of the causative organism.

In pediatric patients as for adults, the creatinine clearance should be adjusted for body surface area or lean body mass, and the dosing frequency should be reduced in cases of renal insufficiency.

In patients undergoing hemodialysis, a loading dose of 1 gram is recommended, followed by 1 gram after each hemodialysis period.

FORTAZ can also be used in patients undergoing intraperitoneal dialysis and continuous ambulatory peritoneal dialysis. In such patients, a loading dose of 1 gram of FORTAZ may be given, followed by 500 mg every 24 hours. In addition to IV use, FORTAZ can be incorporated in the dialysis fluid at a concentration of 250 mg for 2 L of dialysis fluid.

Note: Generally FORTAZ should be continued for 2 days after the signs and symptoms of infection have disappeared, but in complicated infections longer therapy may be required.

Administration

FORTAZ may be given intravenously or by deep IM injection into a large muscle mass such as the upper outer quadrant of the gluteus maximus or lateral part of the thigh. Intra-arterial administration should be avoided (see PRECAUTIONS).

Intramuscular Administration

For IM administration, FORTAZ should be constituted with one of the following diluents: Sterile Water for Injection, Bacteriostatic Water for Injection, or 0.5% or 1% Lidocaine Hydrochloride Injection. Refer to Table 5.

Intravenous Administration

The IV route is preferable for patients with bacterial septicemia, bacterial meningitis, peritonitis, or other severe or life-threatening infections, or for patients who may be poor risks because of lowered resistance resulting from such debilitating conditions as malnutrition, trauma, surgery, diabetes, heart failure, or malignancy, particularly if shock is present or pending.

For direct intermittent IV administration, constitute FORTAZas directed in Table 5 with Sterile Water for Injection. Slowly inject directly into the vein over a period of 3 to 5 minutes or give through the tubing of an administration set while the patient is also receiving one of the compatible IV fluids (see COMPATIBILITY AND STABILITY).

For IV infusion, constitute the 500-mg, 1-gram, or 2-gram vial and add an appropriate quantity of the resulting solution to an IV container with one of the compatible IV fluids listed under the COMPATIBILITY AND STABILITY section.

Intermittent IV infusion with a Y-type administration set can be accomplished with compatible solutions. However, during infusion of a solution containing ceftazidime, it is desirable to discontinue the other solution.

Table 5. Preparation of Solutions of FORTAZ
Size | Amount of Diluent to be Added; (mL) | Approximate Available Volume; (mL) | Approximate Ceftazidime Concentration; (mg/mL)
Intramuscular
500-mg vial | 1.5 | 1.8 | 280
1-gram vial | 3 | 3.6 | 280
Intravenous
500-mg vial | 5.3 | 5.7 [To obtain a dose of 500 mg, withdraw 5 mL from the vial following reconstitution.] | 100
1-gram vial | 10 | 10.8 [To obtain a dose of 1 g, withdraw 10 mL from the vial following reconstitution.] | 100
2-gram vial | 10 | 11.5 [To obtain a dose of 2 g, withdraw 11.5 mL from the vial following reconstitution.] | 170

All vials of FORTAZ as supplied are under reduced pressure. When FORTAZ is dissolved, carbon dioxide is released and a positive pressure develops. For ease of use please follow the recommended techniques of constitution described on the detachable Instructions for Constitution section of this insert.

Solutions of FORTAZ, like those of most beta-lactam antibacterial drugs, should not be added to solutions of aminoglycoside antibacterial drugs because of potential interaction.

However, if concurrent therapy with FORTAZ and an aminoglycoside is indicated, each of these antibacterial drugs can be administered separately to the same patient.

COMPATIBILITY AND STABILITY

Intramuscular

FORTAZ, when constituted as directed with Sterile Water for Injection, Bacteriostatic Water for Injection, or 0.5% or 1% Lidocaine Hydrochloride Injection, maintains satisfactory potency for 12 hours at room temperature or for 3 days under refrigeration. Solutions in Sterile Water for Injection that are frozen immediately after constitution in the original container are stable for 3 months when stored at -20°C. Once thawed, solutions should not be refrozen. Thawed solutions may be stored for up to 3 hours at room temperature or for 3 days in a refrigerator.

Intravenous

FORTAZ, when constituted as directed with Sterile Water for Injection, maintains satisfactory potency for 12 hours at room temperature or for 3 days under refrigeration.

FORTAZ is compatible with the more commonly used IV infusion fluids. Solutions at concentrations between 1 and 40 mg/mL in 0.9% Sodium Chloride Injection; 1/6 M Sodium Lactate Injection; 5% Dextrose Injection; 5% Dextrose and 0.225% Sodium Chloride Injection; 5% Dextrose and 0.45% Sodium Chloride Injection; 5% Dextrose and 0.9% Sodium Chloride Injection; 10% Dextrose Injection; Ringer's Injection, USP; Lactated Ringer's Injection, USP; 10% Invert Sugar in Water for Injection; and NORMOSOL®-M in 5% Dextrose Injection may be stored for up to 12 hours at room temperature or for 3 days if refrigerated.

FORTAZ is less stable in Sodium Bicarbonate Injection than in other IV fluids. It is not recommended as a diluent. Solutions of FORTAZ in 5% Dextrose Injection and 0.9% Sodium Chloride Injection are stable for at least 6 hours at room temperature in plastic tubing, drip chambers, and volume control devices of common IV infusion sets.

Ceftazidime at a concentration of 4 mg/mL has been found compatible for 12 hours at room temperature or for 3 days under refrigeration in 0.9% Sodium Chloride Injection or 5% Dextrose Injection when admixed with: cefuroxime sodium (ZINACEF®) 3 mg/mL, heparin 10 or 50 U/mL, or potassium chloride 10 or 40 mEq/L.

Vancomycin solution exhibits a physical incompatibility when mixed with a number of drugs, including ceftazidime. The likelihood of precipitation with ceftazidime is dependent on the concentrations of vancomycin and ceftazidime present. It is therefore recommended, when both drugs are to be administered by intermittent IV infusion, that they be given separately, flushing the IV lines (with 1 of the compatible IV fluids) between the administration of these 2 agents.

Note: Parenteral drug products should be inspected visually for particulate matter before administration whenever solution and container permit.

As with other cephalosporins, FORTAZ powder, as well as solutions, tend to darken depending on storage conditions; within the stated recommendations, however, product potency is not adversely affected.

HOW SUPPLIED

FORTAZ® in the dry state should be stored between 15° and 30°C (59° and 86°F) and protected from light. FORTAZ® is a dry, white to off-white powder supplied in vials as follows:

- NDC 52565-105-10 500-mg* Single-Dose Vial (Carton of 10)
- NDC 52565-106-10 1-g* Single-Dose Vial (Carton of 10)
- NDC 52565-107-10 2-g* Single-Dose Vial (Carton of 10)

*Equivalent to anhydrous ceftazidime.

REFERENCES

1. Cockcroft DW, Gault MH. Prediction of creatinine clearance from serum creatinine. Nephron. 1976;16:31-41.

FORTAZ® AND ZINACEF® are registered trademarks of Teligent, Inc.
CLINITEST® and CLINISTIX® are registered trademarks of Ames Division, Miles Laboratories, Inc.

Manufactured by:
Astral SteriTech Pvt. Ltd.
India
Distributed by:
Teligent Pharma, Inc.
Buena, NJ 08310

PI-FOR-00
Rev 02/2019

_ _ _ _ _ _ _ _ _ _ _ _ _ _ _ _ _ _ _ _ _ _ _ _ _ _ _ _ _ _ _ _ _ _ _ _ _ _ _ _ _ _ _ _ _ _ _

TEAR AWAY

FORTAZ®

(ceftazidime for injection)

Instructions for Constitution

Vials: 500 mg IM/IV, 1 g IM/IV, 2 g IV

1. Insert the syringe needle through the vial closure and inject the recommended volume of diluent. The vacuum may assist entry of the diluent. Remove the syringe needle.
2. Shake to dissolve; a clear solution will be obtained in 1 to 2 minutes.
3. Invert the vial. Ensuring that the syringe plunger is fully depressed, insert the needle through the vial closure and withdraw the total volume of solution into the syringe (the pressure in the vial may aid withdrawal). Ensure that the needle remains within the solution and does not enter the headspace. The withdrawn solution may contain some bubbles of carbon dioxide.

Note: As with the administration of all parenteral products, accumulated gases should be expressed from the syringe immediately before injection of FORTAZ.

Manufactured by:
Astral SteriTech Pvt. Ltd.
India
Distributed by:
Teligent Pharma, Inc.
Buena, NJ 08310
PI-FOR-00
Rev 02/2019

PACKAGE LABEL.PRINCIPAL DISPLAY PANEL - 500 mg Vial

NDC 52565-105-01
Fortaz®
(ceftazidime for
injection)
500 mg/Vial
Equivalent to 500 mg of anhydrous
ceftazidime.
For intramuscular or
intravenous use
Rx only

PACKAGE LABEL.PRINCIPAL DISPLAY PANEL - 1 g Vial

NDC 52565-106-01
Fortaz® (ceftazidime for injection)
1 g/Vial
Equivalent to 1 g of anhydrous
ceftazidime.
For intramuscular or
intravenous use
Rx only

PACKAGE LABEL.PRINCIPAL DISPLAY PANEL - 2 g Vial

NDC 52565-107-01
Fortaz® (ceftazidime for injection)
2 g/Vial
Equivalent to 2 g of anhydrous
ceftazidime.
For intravenous use
Rx only